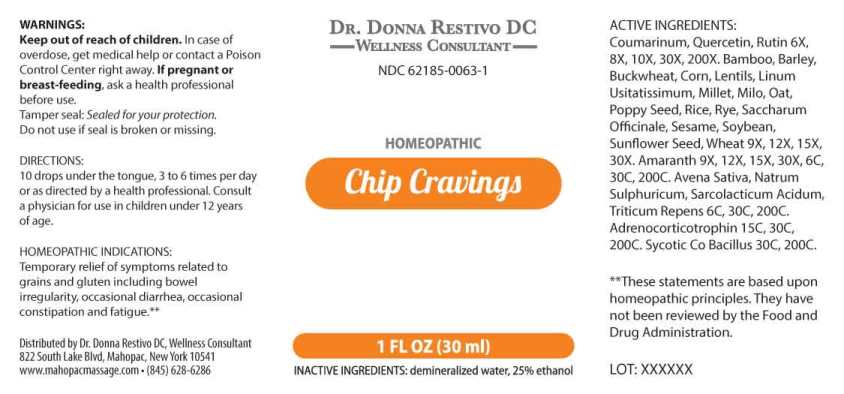 DRUG LABEL: Chip Cravings
NDC: 62185-0063 | Form: LIQUID
Manufacturer: Dr. Donna Restivo DC
Category: homeopathic | Type: HUMAN OTC DRUG LABEL
Date: 20230110
DEA Schedule: CII

ACTIVE INGREDIENTS: COUMARIN 6 [hp_X]/1 mL; QUERCETIN 6 [hp_X]/1 mL; RUTIN 6 [hp_X]/1 mL; BAMBUSA VULGARIS LEAF 9 [hp_X]/1 mL; BARLEY 9 [hp_X]/1 mL; POPPY SEED 9 [hp_X]/1 mL; CORN 9 [hp_X]/1 mL; FLAX SEED 9 [hp_X]/1 mL; BUCKWHEAT 9 [hp_X]/1 mL; MILLET 9 [hp_X]/1 mL; SORGHUM BICOLOR WHOLE 9 [hp_X]/1 mL; OAT 9 [hp_X]/1 mL; BROWN RICE 9 [hp_X]/1 mL; RYE 9 [hp_X]/1 mL; LENTIL 9 [hp_X]/1 mL; SESAME SEED 9 [hp_X]/1 mL; AMARANTH 9 [hp_X]/1 mL; SOYBEAN 9 [hp_X]/1 mL; SUCROSE 9 [hp_X]/1 mL; SUNFLOWER SEED 9 [hp_X]/1 mL; WHEAT 9 [hp_X]/1 mL; AVENA SATIVA FLOWERING TOP 6 [hp_C]/1 mL; SODIUM SULFATE 6 [hp_C]/1 mL; LACTIC ACID, L- 6 [hp_C]/1 mL; ELYMUS REPENS ROOT 6 [hp_C]/1 mL; CORTICOTROPIN 15 [hp_C]/1 mL; ENTEROCOCCUS FAECALIS 30 [hp_C]/1 mL
INACTIVE INGREDIENTS: WATER; ALCOHOL

DRUG FACTS:

ACTIVE INGREDIENTS:

Coumarinum 6X, 8X, 10X, 30X, 200X, Quercetin 6X, 8X, 10X, 30X, 200X, Rutin 6X, 8X, 10X, 30X, 200X, Bamboo 9X, 12X, 15X, 30X, Barley 9X, 12X, 15X, 30X, Poppy seed 9X, 12X, 15X, 30X, Corn 9X, 12X, 15X, 30X, Flax Seed 9X, 12X, 15X, 30X, Buckwheat 9X, 12X, 15X, 30X, Millet 9X, 12X, 15X, 30X, Milo 9X, 12X, 15X, 30X, Oat 9X, 12X, 15X, 30X, Rice 9X, 12X, 15X, 30X, Rye 9X, 12X, 15X, 30X, Lentils 9X, 12X, 15X, 30X, Sesame 9X, 12X, 15X, 30X, Amaranth 9X, 12X, 15X, 30X, Soybean 9X, 12X, 15X, 30X, Saccharum Officinale 9X, 12X, 15X, 30X, Sunflower Seed 9X, 12X, 15X, 30X, Wheat 9X, 12X, 15X, 30X, Amaranth 6C, 30C, 200C, Avena Sativa 6C, 30C, 200C, Natrum Sulphuricum 6C, 30C, 200C, Sarcolacticum Acidum 6C, 30C, 200C, Triticum Repens 6C, 30C, 200C, Adrenocorticotrophin 15C, 30C, 200C, Sycotic Co Bacillus 30C, 200C.

HOMEOPATHIC INDICATIONS:

Temporary relief of symptoms related to grains and gluten including bowel irregularity, occasional diarrhea, occasional constipation and fatigue.**

**These statements are based upon homeopathic principles. They have not been reviewed by the Food and Drug Administration.

WARNINGS:

Keep out of reach of children. In case of overdose, get medical help or contact a Poison Control Center right away.

If pregnant or breast-feeding, ask a health professional before use.

Tamper seal: Sealed for your protection. Do not use if seal is broken or missing.

Keep out of reach of children. In case of overdose, get medical help or contact a Poison Control Center right away.

DIRECTIONS:

10 drops under the tongue, 3 to 6 times per day or as directed by a health professional. Consult a physician for use in children under 12 years of age.

HOMEOPATHIC INDICATIONS:

Temporary relief of symptoms related to grains and gluten including bowel irregularity, occasional diarrhea, occasional constipation and fatigue.**

**These statements are based upon homeopathic principles. They have not been reviewed by the Food and Drug Administration.

INACTIVE INGREDIENTS:

demineralized water, 25% ethanol

QUESTIONS:

Distributed by Dr. Donna Restivo DC, Wellness Consultant

822 South Lake Blvd, Mahopac, New York 10541

www.mahopacmassage.com • (845)628-6286

PACKAGE LABEL DISPLAY:

DR. DONNA RESTIVO DC
WELLNESS CONSULTANT
NDC 62185-0063-1
HOMEOPATHIC
Chip Cravings
1 FL OZ (30 ml)